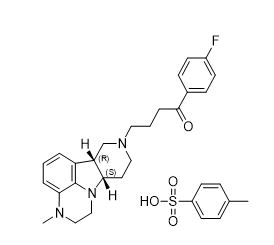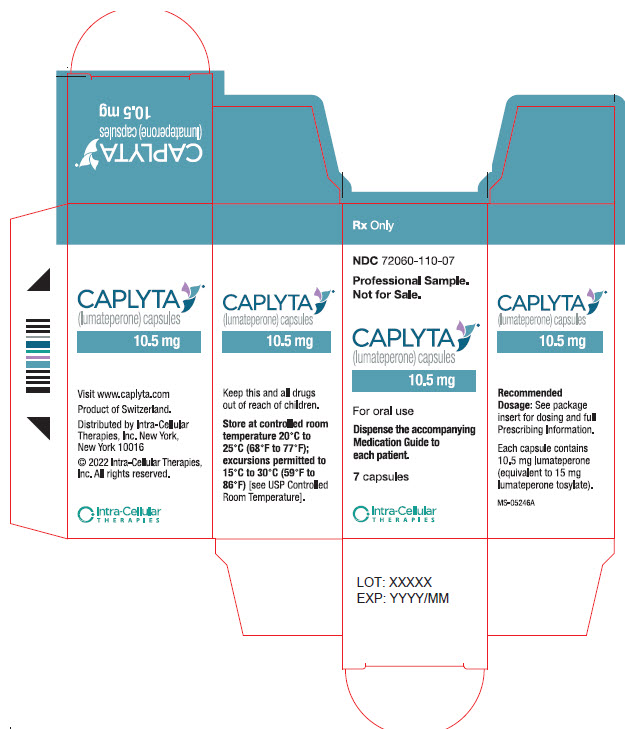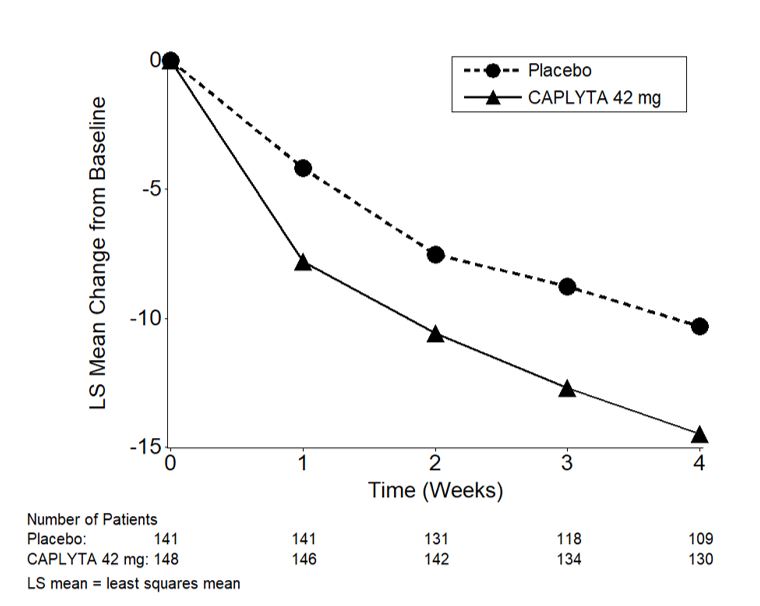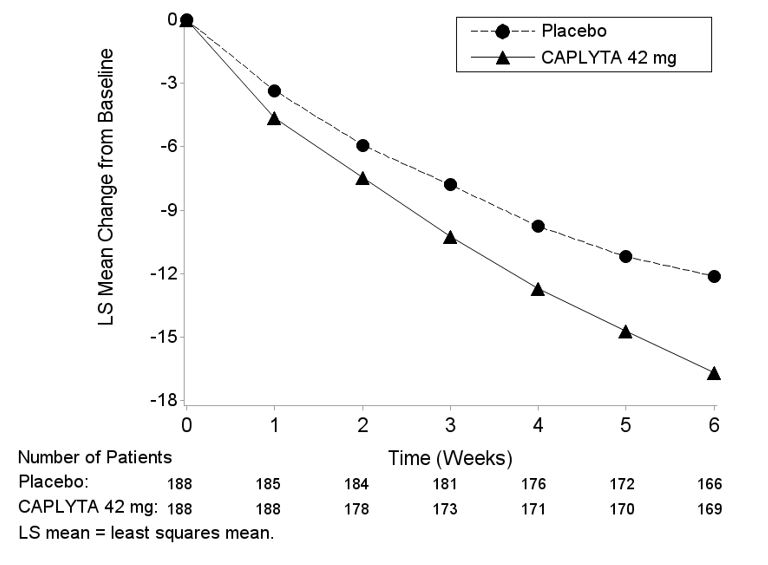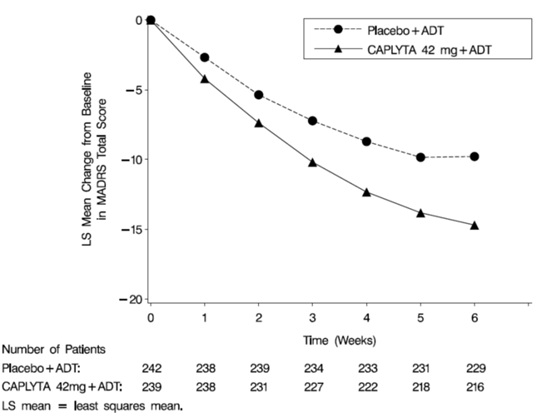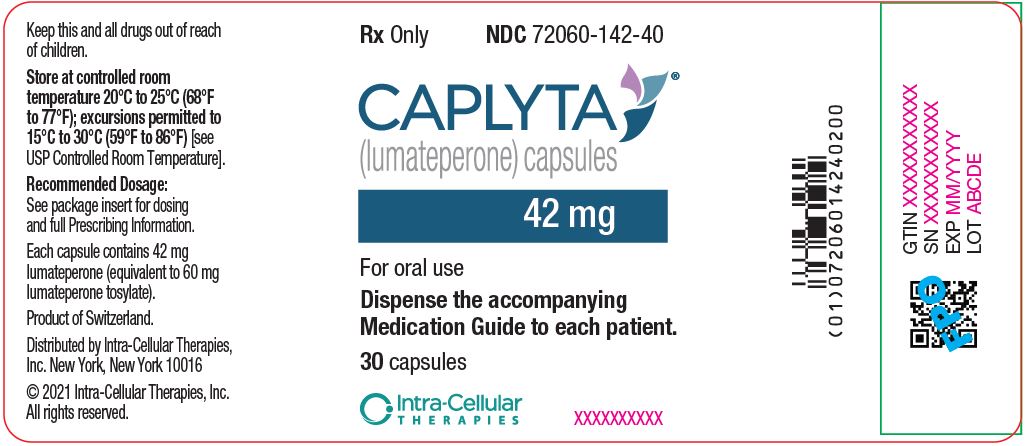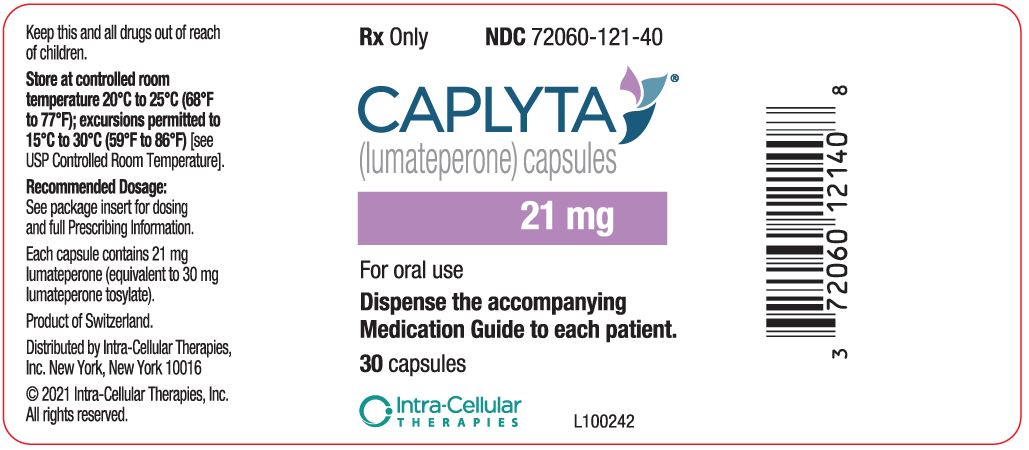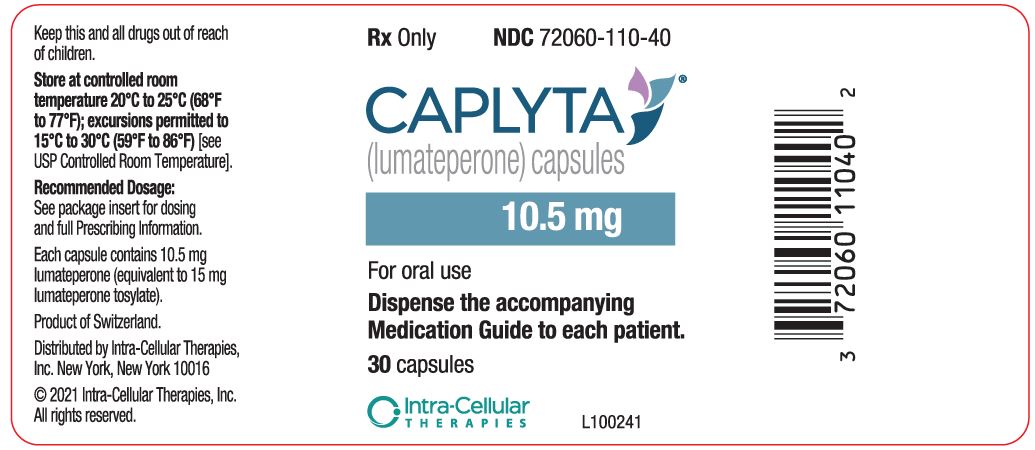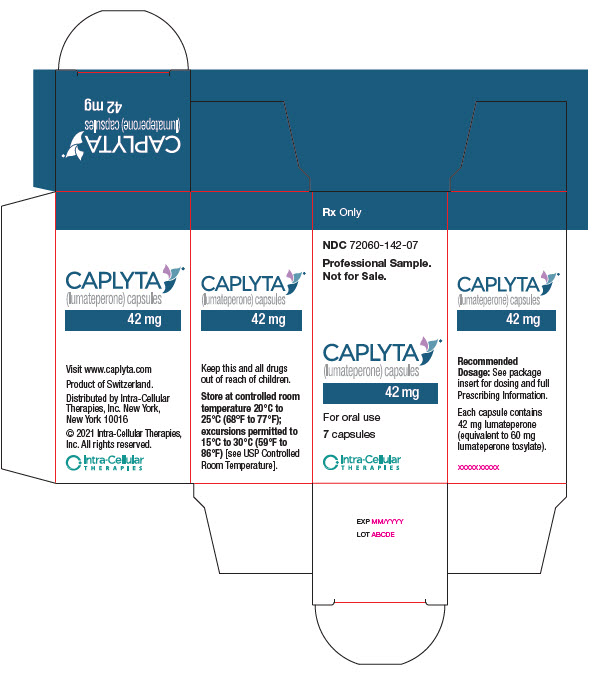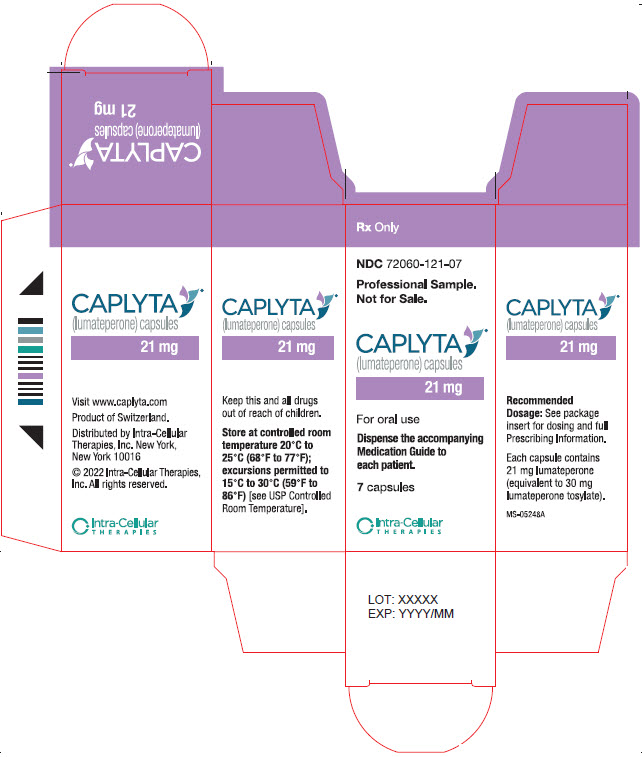 DRUG LABEL: CAPLYTA
NDC: 72060-142 | Form: CAPSULE
Manufacturer: Intra-Cellular Therapies, Inc
Category: prescription | Type: HUMAN PRESCRIPTION DRUG LABEL
Date: 20251114

ACTIVE INGREDIENTS: LUMATEPERONE 42 mg/1 1
INACTIVE INGREDIENTS: MANNITOL; CROSCARMELLOSE SODIUM; TALC; MAGNESIUM STEARATE; GELATIN

HIGHLIGHTS OF PRESCRIBING INFORMATION

These highlights do not include all the information needed to use CAPLYTA safely and effectively. See full prescribing information for CAPLYTA.
CAPLYTA® (lumateperone) capsules, for oral use
Initial U.S. Approval: 2019

WARNING: INCREASED MORTALITY IN ELDERLY PATIENTS WITH DEMENTIA-RELATED PSYCHOSIS; and SUICIDAL THOUGHTS AND BEHAVIORS

See full prescribing information for complete boxed warning.

- Elderly patients with dementia-related psychosis treated with antipsychotic drugs are at an increased risk of death. CAPLYTA is not approved for the treatment of patients with dementia-related psychosis. (5.1)

- Antidepressants increased the risk of suicidal thoughts and behaviors in pediatric and young adult patients. Closely monitor all antidepressant-treated patients for worsening and emergence of suicidal thoughts and behaviors. Safety and effectiveness of CAPLYTA have not been established in pediatric patients. (5.2, 8.4)

RECENT MAJOR CHANGES

Indications and Usage, adjunctive treatment of major depressive disorder (1) 11/2025

1 INDICATIONS AND USAGE

CAPLYTA is an atypical antipsychotic indicated for:

- Treatment of schizophrenia in adults. (1)
- Treatment of depressive episodes associated with bipolar I or II disorder (bipolar depression) in adults, as monotherapy and as adjunctive therapy with lithium or valproate. (1)
- Adjunctive therapy with antidepressants for the treatment of major depressive disorder (MDD) in adults. (1)

2 DOSAGE AND ADMINISTRATION

- Recommended oral dosage of CAPLYTA is 42 mg once daily with or without food. (2.1)
- Moderate hepatic impairment or severe hepatic impairment: Recommended dosage is 21 mg once daily. (2.3, 8.6)

3 DOSAGE FORMS AND STRENGTHS

Capsules: 42 mg, 21 mg, 10.5 mg (3)

4 CONTRAINDICATIONS

CAPLYTA is contraindicated in patients with history of hypersensitivity reaction to lumateperone or any components of CAPLYTA. (4)

5 WARNINGS AND PRECAUTIONS

- Cerebrovascular Adverse Reactions in Elderly Patients with Dementia-Related Psychosis: Increased incidence of cerebrovascular adverse reactions (e.g., stroke and transient ischemic attack). (5.3)
- Neuroleptic Malignant Syndrome: If NMS is suspected, immediately discontinue CAPLYTA and provide intensive symptomatic treatment and monitoring. (5.4)
- Tardive Dyskinesia: If signs and symptoms of TD occur consider discontinuing CAPLYTA treatment. (5.5)
- Metabolic Changes: Monitor for hyperglycemia/diabetes mellitus, dyslipidemia, and weight gain. (5.6)
- Leukopenia, Neutropenia, and Agranulocytosis: In patients with pre-existing low white blood cell count (WBC) or history of leukopenia or neutropenia, perform complete blood counts (CBC). Consider discontinuing CAPLYTA if clinically significant decline in WBC occurs in absence of other causative factors. Discontinue CAPLYTA in patients with clinically significant neutropenia or ANC < 1000/mm^3 and monitor closely until the neutropenia resolve. (5.7)
- Orthostatic Hypotension and Syncope: Monitor heart rate and blood pressure in patients who are vulnerable to hypotension. (5.8)
- Seizures: Use cautiously in patients with a history of seizures or with other conditions that lower seizure threshold. (5.10)
- Potential for Cognitive and Motor Impairment: Use caution when operating machinery and driving a motor vehicle until patients are reasonably certain that therapy with CAPLYTA does not affect them adversely. (5.11)

6 ADVERSE REACTIONS

Most common adverse reactions in clinical trials (incidence > 5% and greater than twice placebo) were (6.1):

- Schizophrenia: somnolence/sedation and dry mouth.
- Bipolar depression: somnolence/sedation, dizziness, nausea, dry mouth.
- MDD: dizziness, dry mouth, somnolence/sedation, nausea, fatigue, diarrhea.

To report SUSPECTED ADVERSE REACTIONS, contact Intra-Cellular Therapies, Inc. at 1-888-611-4824 or FDA at 1-800-FDA-1088 or www.fda.gov/medwatch.

7 DRUG INTERACTIONS

- CYP3A4 inducers: Avoid concomitant use with CAPLYTA. (7.1)
- Strong CYP3A4 inhibitors: Recommended dosage is 10.5 mg once daily. (2.2, 7.1)
- Moderate CYP3A4 inhibitors: Recommended dosage is 21 mg once daily. (2.2, 7.1)

8 USE IN SPECIFIC POPULATIONS

Pregnancy: May cause extrapyramidal and/or withdrawal symptoms in neonates with third trimester exposure. (8.1)

FULL PRESCRIBING INFORMATION

WARNING: INCREASED MORTALITY IN ELDERLY PATIENTS WITH DEMENTIA-RELATED PSYCHOSIS; and SUICIDAL THOUGHTS AND BEHAVIORS

Increased Mortality in Elderly Patients with Dementia-Related Psychosis

Elderly patients with dementia-related psychosis treated with antipsychotic drugs are at an increased risk of death. CAPLYTA is not approved for the treatment of patients with dementia-related psychosis [see Warnings and Precautions (5.1)].

Suicidal Thoughts and Behaviors

Antidepressants increased the risk of suicidal thoughts and behaviors in pediatric and young adults in short-term studies. Closely monitor all antidepressant-treated patients for clinical worsening, and for emergence of suicidal thoughts and behaviors [see Warnings and Precautions (5.2)]. The safety and effectiveness of CAPLYTA have not been established in pediatric patients [see Use in Specific Populations (8.4)].

RECENT MAJOR CHANGES

- Indications and Usage, adjunctive treatment of major depressive disorder (1) 11/2025

1 INDICATIONS AND USAGE

CAPLYTA is indicated for:

- Treatment of schizophrenia in adults [see Clinical Studies (14.1)].
- Treatment of depressive episodes associated with bipolar I or II disorder (bipolar depression) in adults, as monotherapy and as adjunctive therapy with lithium or valproate [see Clinical Studies (14.2)].
- Adjunctive therapy with antidepressants for the treatment of major depressive disorder (MDD) in adults [see Clinical Studies (14.3)].

2 DOSAGE AND ADMINISTRATION

2.1 Recommended Dosage

The recommended CAPLYTA dosage is 42 mg administered orally once daily with or without food. Dose titration is not needed.

2.2 Dosage Recommendations for Concomitant Use with Moderate or Strong CYP3A4 Inhibitors

The recommended CAPLYTA dosage in patients who receive [see Drug Interactions (7.1)]:

- Strong CYP3A4 inhibitors is 10.5 mg once daily.
- Moderate CYP3A4 inhibitors is 21 mg once daily.

2.3 Dosage Recommendations for Patients with Hepatic Impairment

For patients with moderate hepatic impairment (HI) (Child-Pugh class B) or severe HI (Child-Pugh class C), the recommended CAPLYTA dosage is 21 mg once daily [see Use in Specific Populations (8.6)]. The recommended CAPLYTA dosage in patients with mild HI is the same as those with normal hepatic function.

3 DOSAGE FORMS AND STRENGTHS

CAPLYTA capsules are available in three strengths:

- 42 mg: Blue cap and opaque white body imprinted with “ITI-007 42 mg”
- 21 mg: Opaque white cap and body imprinted with “ITI-007 21 mg”
- 10.5 mg: Opaque light pink cap and body imprinted with “ITI-007 10.5 mg”

4 CONTRAINDICATIONS

CAPLYTA is contraindicated in patients with history of hypersensitivity reaction to lumateperone or any components of CAPLYTA. Reactions have included pruritus, rash (e.g. allergic dermatitis, papular rash, and generalized rash), and urticaria.

5 WARNINGS AND PRECAUTIONS

5.1 Increased Mortality in Elderly Patients with Dementia-Related Psychosis

Elderly patients with dementia-related psychosis treated with antipsychotic drugs are at an increased risk of death. In an analysis of 17 placebo-controlled trials (modal duration of 10 weeks), largely in patients taking atypical antipsychotic drugs, the risk of death in antipsychotic drug-treated patients was 1.6 to 1.7 times the risk of death in placebo-treated patients. Over the course of a typical 10-week controlled trial, the incidence of death in antipsychotic-treated patients was about 4.5%, compared to an incidence of about 2.6% in placebo-treated patients. Although the causes of death varied, most of the deaths appeared to be either cardiovascular (e.g., heart failure, sudden death) or infectious (e.g., pneumonia).

CAPLYTA is not approved for the treatment of patients with dementia-related psychosis [see Indications and Usage (1)].

5.2 Suicidal Thoughts and Behaviors in Pediatric and Young Adult Patients

In pooled analyses of placebo-controlled trials of antidepressant drugs (SSRIs and other antidepressant classes) that included approximately 77,000 adult patients and 4,500 pediatric patients, the incidence of suicidal thoughts and behaviors in antidepressant-treated pediatric and young adult patients was greater than in placebo-treated patients. There were differences in absolute risk of suicidal thoughts and behaviors across the different uses, with the highest incidence in patients with MDD. The drug-placebo differences in the number of cases of suicidal thoughts and behaviors per 1,000 patients treated are provided in Table 1.

Table 1: Risk Differences of the Number of Patients with Suicidal Thoughts and Behaviors in the Pooled Placebo-Controlled Trials of Antidepressants in Pediatric* and Adult Patients
Age Range | Drug-Placebo Difference in Number of Patients of Suicidal Thoughts; or Behaviors per 1000 Patients Treated
 | Increases Compared to Placebo
<18 years old | 14 additional patients
18-24 years old | 5 additional patients
 | Decreases Compared to Placebo
25-64 years old | 1 fewer patient
>65 years old | 6 fewer patients

*CAPLYTA is not approved for use in pediatric patients.

It is unknown whether the risk of suicidal thoughts and behaviors in pediatric and young adult patients extends to longer-term use, i.e., beyond four months. However, there is substantial evidence from placebo-controlled maintenance trials in adults with MDD that antidepressants delay the recurrence of depression and that depression itself is a risk factor for suicidal thoughts and behaviors.

Monitor all antidepressant-treated patients, especially during the initial few months of anti-depressant drug therapy, and at times of dosage changes. Counsel family members or caregivers of patients to monitor for changes in behavior and to alert the health care provider. Consider changing the therapeutic regimen, including possibly discontinuing CAPLYTA, in patients whose depression is persistently worse, or who experience suicidal thoughts or behaviors.

5.3 Cerebrovascular Adverse Reactions, Including Stroke, in Elderly Patients with Dementia-Related Psychosis

In placebo-controlled trials, elderly patients with dementia-related psychosis treated with antipsychotics had a higher incidence of stroke and transient ischemic attack, including fatal stroke compared to those treated with placebo.

CAPLYTA is not approved for the treatment of patients with dementia-related psychosis [see Indications and Usage (1)].

5.4 Neuroleptic Malignant Syndrome

Neuroleptic Malignant Syndrome (NMS), a potentially fatal symptom complex, has been reported in association with administration of antipsychotic drugs. Clinical manifestations of NMS include hyperpyrexia, muscle rigidity, delirium, and autonomic instability. Additional signs may include elevated creatine phosphokinase, myoglobinuria (rhabdomyolysis), and acute renal failure.

If NMS is suspected, immediately discontinue CAPLYTA and provide intensive symptomatic treatment and monitoring.

5.5 Tardive Dyskinesia

Tardive dyskinesia (TD) may develop in patients treated with antipsychotic drugs, including CAPLYTA. TD can develop after a relatively brief treatment period at low dosages and may also occur after discontinuation of treatment. If antipsychotic treatment is discontinued, TD may partially or completely remit. Antipsychotic treatment, however, may suppress or partially suppress the signs and symptoms of TD, and may mask the underlying process. The effect that symptomatic suppression has upon the long-term course of TD is unknown.

The TD risk appears to be highest among the elderly, especially elderly women, but it is not possible to predict which patients are likely to develop TD. The TD risk and the likelihood that TD will become irreversible increase with the duration of antipsychotic drug treatment and the cumulative dosage.

Periodically reassess the need for continued treatment. If signs and symptoms of TD appear in CAPLYTA-treated patients, consider drug discontinuation. However, some patients may require CAPLYTA treatment despite the presence of TD.

5.6 Metabolic Changes

Antipsychotic drugs have caused metabolic changes, including hyperglycemia, diabetes mellitus, dyslipidemia, and weight gain.

Hyperglycemia and Diabetes Mellitus

Hyperglycemia, in some cases extreme and associated with ketoacidosis, hyperosmolar coma or death, has been reported in patients treated with antipsychotics. There have been reports of hyperglycemia in patients treated with CAPLYTA. Assess fasting plasma glucose before or soon after initiation of CAPLYTA and monitor periodically during long-term treatment.

- In pooled data from short-term (4- to 6-week), placebo-controlled trials of adult patients with schizophrenia, mean changes from baseline and the proportion of patients with shifts from normal to greater than normal levels of fasting glucose were similar in CAPLYTA-treated and placebo-treated patients. In an uncontrolled open-label trial of CAPLYTA for up to 1 year in adult patients with stable schizophrenia, the percentages of patients with shifts in fasting glucose and insulin values from normal to high were 8% and 12%, respectively. In this trial, 5% of CAPLYTA-treated patients with normal hemoglobin A1c (<6.5%) at baseline developed elevated levels (≥6.5%) post-baseline.
- In data from short-term (6-week), placebo-controlled monotherapy and adjunctive therapy bipolar depression trials, mean changes from baseline and the proportion of patients with shifts from normal to greater than normal levels of fasting glucose and insulin were similar in CAPLYTA-treated and placebo-treated patients.
- In pooled data from short-term (6-week), placebo-controlled adjunctive therapy MDD trials, mean changes from baseline and the proportion of patients with shifts from normal to greater than normal levels of fasting glucose were similar in CAPLYTA-treated and placebo-treated patients.

Dyslipidemia

Antipsychotics have caused adverse alterations in lipids. Before or soon after initiation of antipsychotic medications, obtain a fasting lipid profile at baseline and monitor periodically during treatment.

- In pooled data from short-term (4- to 6-week), placebo-controlled trials of adult patients with schizophrenia, mean changes from baseline and the proportion of patients with shifts to higher levels of fasting total cholesterol and triglycerides were similar in CAPLYTA-treated and placebo-treated patient. In an uncontrolled open-label trial of CAPLYTA for up to 1 year in patients with stable schizophrenia, the percentages of patients with a shift from normal to high were 8%, 5%, and 4% for total cholesterol, triglycerides, and LDL cholesterol, respectively.
- In data from short-term (6-week), placebo-controlled monotherapy and adjunctive therapy bipolar depression trials, mean changes from baseline and the proportion of patients with shifts to higher levels of fasting total cholesterol and triglycerides were similar in CAPLYTA-treated and placebo-treated patients. In an uncontrolled open-label trial of CAPLYTA for up to 6 months in patients with bipolar depression, the proportion of patients with a shift from normal to high were 10%, 5%, and 2% for total cholesterol, triglycerides, and LDL cholesterol, respectively.
- In pooled data from short-term (6-week), placebo-controlled adjunctive therapy MDD trials, mean changes from baseline and the proportion of patients with shifts to higher levels of fasting total cholesterol and triglycerides were similar in CAPLYTA-treated and placebo-treated patients.

Weight Gain

Weight gain has been observed with use of antipsychotics. Monitor weight at baseline and frequently thereafter.

- In pooled data from placebo-controlled trials of adult patients with schizophrenia, mean changes from baseline and the proportion of patients with an increase in weight ≥7% from baseline to end of study was similar in CAPLYTA-treated and placebo-treated patients. In an uncontrolled open-label trial of CAPLYTA for up to one year in patients with stable schizophrenia, the mean change in body weight was approximately -2 kg (SD 5.6) at Day 175 and approximately - 3.2 kg (SD 7.4) at Day 350.
- In data from short-term (6-week), placebo-controlled monotherapy and adjunctive therapy bipolar depression trials, mean changes from baseline and the proportion of patients with an increase in weight ≥7% from baseline to end of study were similar in CAPLYTA-treated and placebo-treated patients. In an uncontrolled open-label trial of CAPLYTA for up to 6 months in patients with bipolar depression, the mean change in body weight was -0.01 kg (SD 3.1) at Day 175.
- In pooled data from short-term (6-week), placebo-controlled adjunctive therapy MDD trials, mean changes from baseline and the proportion of patients with an increase in weight ≥7% from baseline to end of study were similar in CAPLYTA-treated and placebo-treated patients.
- In a long-term open-label adjunctive therapy MDD trial of CAPLYTA for up to 6 months, the mean change in body weight was -0.16 kg (SD 3.7) at Week 26.

5.7 Leukopenia, Neutropenia, and Agranulocytosis

Leukopenia and neutropenia have been reported during treatment with antipsychotic drugs, including CAPLYTA. Agranulocytosis (including fatal cases) has been reported with other antipsychotic drugs.

Possible risk factors for antipsychotic drug-leukopenia and neutropenia include pre-existing low white blood cell count (WBC) or absolute neutrophil count (ANC) and history of drug-induced leukopenia or neutropenia.

In patients with a pre-existing low WBC or ANC or a history of drug-induced leukopenia or neutropenia, perform complete blood count (CBC) monitoring during the first few months of CAPLYTA therapy. Consider discontinuing CAPLYTA in patients who have a clinically significant decline in WBC in the absence of other causative factors. Discontinue CAPLYTA in patients with clinically significant neutropenia or ANC < 1000/mm^3 and monitor closely until the neutropenia resolves.

5.8 Orthostatic Hypotension and Syncope

Atypical antipsychotics cause orthostatic hypotension and syncope. Generally, the risk is greatest during initial dose administration.

Orthostatic vital signs should be monitored in patients who are vulnerable to hypotension (e.g., elderly patients, patients with dehydration, hypovolemia, and concomitant treatment with antihypertensive drugs), patients with known cardiovascular disease (history of myocardial infarction, ischemic heart disease, heart failure, or conduction abnormalities), and patients with cerebrovascular disease. CAPLYTA has not been evaluated in patients with a recent history of myocardial infarction or unstable cardiovascular disease. Such patients were excluded from pre-marketing clinical trials.

- In pooled data from short-term (4- to 6-week), placebo-controlled schizophrenia trials, the frequencies of orthostatic hypotension in CAPLYTA-treated and placebo-treated patients were 0.7% and 0%, respectively. The incidence of syncope for CAPLYTA-treated and placebo-treated patients were 0.2% and 0.2%.
- In data from short-term (6-week), placebo-controlled monotherapy and adjunctive therapy bipolar depression trials, the frequencies of orthostatic hypotension for CAPLYTA-treated and placebo-treated patients were both 0%. The incidence of syncope for CAPLYTA and placebo were 0.3% and 0.5%, respectively in the monotherapy trials, and there were no reports of syncope in the adjunctive therapy trial.
- In pooled data from short-term (6-week), placebo-controlled adjunctive therapy MDD trials, the frequencies of orthostatic hypotension for CAPLYTA-treated and placebo-treated patients were 6.6% and 6.2%, respectively. The incidence of syncope for CAPLYTA-treated and placebo-treated patients were 0.2% and 0%, respectively.

5.9 Falls

Antipsychotics, including CAPLYTA, may cause somnolence, postural hypotension, and motor and sensory instability, which may lead to falls and, consequently, fractures and other injuries.

If patients have a condition (or take concomitant drugs) that could exacerbate these effects, complete fall risk assessments when initiating CAPLYTA treatment and periodically during long-term treatment.

5.10 Seizures

Like other antipsychotic drugs, CAPLYTA may cause seizures. The risk of antipsychotic drug-associated seizures is greatest in patients with a history of seizures or with conditions that lower the seizure threshold. Conditions that lower the seizure threshold may be more prevalent in older patients.

Use CAPLYTA cautiously in patients with a history of seizures or with other conditions that lower seizure threshold.

5.11 Potential for Cognitive and Motor Impairment

CAPLYTA, like other antipsychotics, may cause somnolence and has the potential to impair judgment, thinking, and motor skills. Patients should be cautioned about operating hazardous machinery and motor vehicles until they are reasonably certain that therapy with CAPLYTA does not affect them adversely.

- In short-term (i.e., 4- to 6-week), placebo-controlled clinical trials of patients with schizophrenia, somnolence and sedation were reported in 24% of CAPLYTA-treated patients, compared to 10% of placebo-treated patients.
- In short term (6-week), placebo-controlled monotherapy and adjunctive therapy bipolar depression clinical trials, somnolence and sedation were reported in 13% of CAPLYTA-treated patients, compared to 3% of placebo-treated patients.
- In short term (6-week), placebo-controlled adjunctive therapy MDD trials, somnolence and sedation were reported in 12% of CAPLYTA-treated patients, compared to 2% of placebo-treated patients.

5.12 Body Temperature Dysregulation

Atypical antipsychotics may disrupt the body’s ability to reduce core body temperature. Strenuous exercise, exposure to extreme heat, dehydration, and anticholinergic drugs may contribute to an elevation in core body temperature. Use CAPLYTA with caution in patients who may experience these conditions.

5.13 Dysphagia

Esophageal dysmotility and aspiration have been associated with antipsychotic drug use. Antipsychotic drugs, including CAPLYTA, should be used cautiously in patients at risk for aspiration.

6 ADVERSE REACTIONS

The following adverse reactions are discussed in detail in other sections of the labeling:

- Increased Mortality in Elderly Patients with Dementia-Related Psychosis [see Boxed Warning, Warnings and Precautions (5.1)]
- Suicidal Thoughts and Behaviors [see Boxed Warning, Warnings and Precautions (5.2)]
- Cerebrovascular Adverse Reactions, Including Stroke, in Elderly Patients with Dementia-related Psychosis [see Warnings and Precautions (5.3)]
- Neuroleptic Malignant Syndrome [see Warnings and Precautions (5.4)]
- Tardive Dyskinesia [see Warnings and Precautions (5.5)]
- Metabolic Changes [see Warnings and Precautions (5.6)]
- Leukopenia, Neutropenia, and Agranulocytosis [see Warnings and Precautions (5.7)]
- Orthostatic Hypotension and Syncope [see Warnings and Precautions (5.8)]
- Falls [see Warnings and Precautions (5.9)]
- Seizures [see Warnings and Precautions (5.10)]
- Potential for Cognitive and Motor Impairment [see Warnings and Precautions (5.11)]
- Body Temperature Dysregulation [see Warnings and Precautions (5.12)]
- Dysphagia [see Warnings and Precautions (5.13)]

6.1 Clinical Trials Experience

Because clinical trials are conducted under widely varying conditions, adverse reaction rates observed in the clinical trials of a drug cannot be directly compared to rates in the clinical trials of another drug and may not reflect the rates observed in practice.

The safety of CAPLYTA has been evaluated in placebo-controlled clinical trials that included 3575 adult patients with schizophrenia, bipolar depression, or major depressive disorder, exposed to one or more CAPLYTA doses. A total of 852 CAPLYTA-treated patients had at least 6 months of treatment and 108 had at least 1 year of treatment with the 42-mg once daily dosage.

Adverse Reactions in Patients with Schizophrenia

The following adverse reactions are based on the pooled short-term (4- to 6-week), placebo-controlled studies in adult patients with schizophrenia in which CAPLYTA was administered at a dosage of 42 mg once daily (N=406) [see Clinical Studies (14.1)].

There was no single adverse reaction that led to discontinuation that occurred at a rate of >2% in CAPLYTA-treated patients. The most common adverse reactions (incidence of at least 5% of CAPLYTA-treated patients and greater than twice the rate of placebo-treated patients) were somnolence/sedation and dry mouth. Adverse reactions (incidence of at least 2% in CAPLYTA-treated patients and greater than in placebo-treated patients) are shown in Table 2.

Table 2: Adverse Reactions Reported in ≥2% of CAPLYTA-Treated Patients and Greater Incidence Than in Placebo-Treated Patients in 4- to 6-week Schizophrenia Trials
 | CAPLYTA; 42 mg; (N=406) | Placebo; (N=412)
Somnolence/Sedation | 24% | 10%
Nausea | 9% | 5%
Dry Mouth | 6% | 2%
Dizziness^1 | 5% | 3%
Creatine Phosphokinase Increased | 4% | 1%
Fatigue | 3% | 1%
Vomiting | 3% | 2%
Hepatic Transaminases Increased^2 | 2% | 1%
Decreased Appetite | 2% | 1%

^1 Dizziness, dizziness postural
^2 ALT, AST, “hepatic enzymes” increased, or liver function test abnormal

Adverse Reactions in Patients with Bipolar Depression (CAPLYTA Monotherapy)

The following adverse reactions are based on the pooled short-term (6-week), placebo-controlled monotherapy bipolar depression studies in adult patients treated with CAPLYTA 42 mg once daily (N=372) [see Clinical Studies (14.2)].

There was no single adverse reaction leading to discontinuation that occurred at a rate of >2% in CAPLYTA-treated patients.

The most common adverse reactions (incidence of at least 5% of CAPLYTA-treated patients and greater than twice the rate in placebo-treated patients) were somnolence/sedation, dizziness, nausea, and dry mouth.

Adverse reactions associated with CAPLYTA (incidence of at least 2% in CAPLYTA-treated patients and greater than placebo-treated patients) are shown in Table 3.

Table 3: Adverse Reactions Reported in ≥2% of CAPLYTA-Treated Patients and Greater Incidence than in Placebo-Treated Patients in Pooled 6-week Monotherapy Bipolar Depression Trials
 | CAPLYTA 42 mg (N=372) | Placebo; (N=374)
Headache | 14% | 8%
Somnolence/Sedation | 13% | 3%
Dizziness^1 | 8% | 4%
Nausea | 8% | 3%
Dry mouth | 5% | 1%
Diarrhea | 4% | 2%
Vomiting | 4% | 0%
Abdominal pain^2 | 2% | 1%
Upper respiratory tract infection | 2% | 1%

^1 Dizziness, dizziness postural
^2 Abdominal discomfort, abdominal pain, abdominal pain upper and lower

Adverse Reactions in Patients with Bipolar Depression (Concomitant Treatment with CAPLYTA and Lithium or Valproate)

The adverse reactions below are based on a 6-week, placebo-controlled adjunctive therapy bipolar depression study in adult patients treated with CAPLYTA 42 mg once daily + lithium or valproate OR placebo + lithium or valproate (N=177) [see Clinical Studies (14.2)].

There was no single adverse reaction leading to discontinuation that occurred at a rate of >2% in patients in the CAPLYTA + lithium or valproate group.

The most common adverse reactions (incidence of at least 5% in patients treated with CAPLYTA + lithium or valproate and greater than twice the rate of patients treated with placebo + lithium or valproate) were somnolence/sedation, dizziness, nausea, and dry mouth.

Adverse reactions associated with CAPLYTA + lithium or valproate (incidence of at least 2% in patients treated with CAPLYTA + lithium or valproate and greater than with patients treated with placebo + lithium or valproate) are shown in Table 4.

Table 4: Adverse Reactions Reported in ≥2% of CAPLYTA-Treated Patients and that Occurred at Greater Incidence than in the Placebo-Treated Patients in a 6-Week Adjunctive Therapy Bipolar Depression Trial
 | CAPLYTA 42 mg + lithium or valproate (N=177) | Placebo + lithium or valproate (N=175)
Somnolence/Sedation | 13% | 3%
Dizziness^1 | 11% | 2%
Nausea | 9% | 4%
Dry mouth | 5% | 1%
Vomiting | 4% | 0%
Diarrhea | 3% | 2%
Upper respiratory tract infection | 3% | 1%
Blurred vision | 3% | 1%
Increased blood prolactin | 2% | 0%

^1 Dizziness, dizziness postural

Adverse Reactions in Studies for Adjunctive Treatment of Major Depressive Disorder

The following adverse reactions are based on pooled short-term (6-week), placebo-controlled adjunctive therapy MDD studies in adult patients treated with CAPLYTA 42 mg orally once daily and background antidepressant therapy (ADT) or placebo and background ADT (N=483) [see Clinical Studies (14.3)].

There was no single adverse reaction leading to discontinuation that occurred at an incidence of >2% in patients treated with CAPLYTA and background ADT.

The most common adverse reactions (incidence of at least 5% of patients treated with CAPLYTA and background ADT and greater than twice the incidence in patients treated with placebo and background ADT) were dizziness, dry mouth, somnolence/sedation, nausea, fatigue, and diarrhea.

Adverse reactions in the adjunctive therapy MDD studies (incidence of at least 2% of patients treated with CAPLYTA and background ADT and greater than in patients treated with placebo and background ADT) are shown in Table 5.

Table 5: Adverse Reactions Reported in ≥2% of Patients Treated with CAPLYTA + Background ADT and at Greater Incidence than in Patients Treated with Placebo + Background ADT in Pooled 6-Week Adjunctive MDD Trials
 | CAPLYTA 42 mg + ADT (N=483) | Placebo + ADT (N=481)
Headache^1 | 19% | 13%
Dizziness^2 | 17% | 5%
Dry Mouth | 13% | 3%
Somnolence/Sedation | 12% | 2%
Nausea | 9% | 4%
Fatigue | 8% | 2%
Diarrhea | 5% | 1%
Tremor | 4% | <1%
Vomiting | 3% | 2%
Vertigo | 3% | <1%
Insomnia | 3% | 2%

^1Headache, migraine, tension headache
^2Dizziness, postural dizziness

Additional Adverse Reactions

Dystonia: Symptoms of dystonia, prolonged abnormal contractions of muscle groups, may occur in susceptible individuals during the first few days of treatment. Dystonic symptoms include: spasm of the neck muscles, sometimes progressing to tightness of the throat, swallowing difficulty, difficulty breathing, and/or protrusion of the tongue. Although these symptoms can occur at low doses, they occur more frequently and with greater severity with high potency and higher doses of first-generation antipsychotic drugs. An elevated risk of acute dystonia is observed in males and younger age groups.

Extrapyramidal Symptoms: In the short-term, placebo-controlled schizophrenia, bipolar depression, and adjunctive MDD studies, extrapyramidal (EPS) symptom data was objectively collected on the Simpson-Angus Scale (SAS) for EPS (total score ranges from 0 to 40), the Barnes Akathisia Rating Scale (BARS) for akathisia (total score ranges from 0 to 14), and the Abnormal Involuntary Movement Scale (AIMS) for dyskinesia (total score ranges from 0 to 28).

- In the 4- to 6-week, placebo-controlled schizophrenia trials, the frequency of EPS-related reported events including akathisia, extrapyramidal disorder, muscle spasms, restlessness, musculoskeletal stiffness, dyskinesia, dystonia, muscle twitching, tardive dyskinesia, tremor, drooling, and involuntary muscle contractions was 6.7% for the CAPLYTA-treated patients and 6.3% for placebo-treated patients. In these trials, the mean changes from baseline for CAPLYTA-treated patients and placebo-treated patients were 0.1 and 0 for the SAS, -0.1 and 0 for the BARS, and 0.1 and 0 for the AIMS, respectively.
- In the 6-week, monotherapy bipolar depression trials, the frequency of reported EPS-related reactions including muscle spasms, dyskinesia, extrapyramidal disorder, movement disorder, tremor, restlessness, and akathisia was 1.3% for CAPLYTA-treated patients and 1.1% for placebo-treated patients. In these trials, the mean changes from baseline for CAPLYTA-treated patients and placebo-treated patients were 0 and 0 for the SAS, -0.1 and -0.1 for the BARS, and 0 and 0 for the AIMS, respectively.
- In a 6-week, adjunctive therapy bipolar depression trial, the frequency of reported EPS-related reactions, including tremor, muscle spasms, akathisia, extrapyramidal disorder, gait disturbance, and restlessness was 4% for CAPLYTA-treated patients and 2.3% for placebo-treated patients. In the 6-week, monotherapy bipolar depression trials, the mean changes from baseline for CAPLYTA-treated patients and placebo-treated patients were 0 and 0 for the SAS, -0.1 and -0.1 for the BARS, and 0 and 0 for the AIMS, respectively. In this trial, the mean changes from baseline for CAPLYTA-treated patients and placebo-treated patients were 0 and 0 for the SAS, 0 and -0.1 for the BARS, and 0 and 0 for the AIMS, respectively.
- In the 6-week, adjunctive MDD trials, the frequency of reported EPS-related adverse reactions (tremor, bradykinesia, muscle spasms, gait disturbance, tongue spasm, muscle tightness and dyskinesia), excluding akathisia and restlessness, was 5% for CAPLYTA-treated patients and 0.8% for placebo-treated patients. The combined incidence of akathisia and restlessness was 1% for CAPLYTA-treated patients and 0.8% for placebo-treated patients. In these trials, the mean changes from baseline for CAPLYTA-treated patients and placebo-treated patients were 0 and 0 for the SAS, 0 and -0.1 for the BARS, and 0 and 0 for the AIMS, respectively.

6.2 Postmarketing Experience

The following adverse reaction has been identified during post-approval use of CAPLYTA. Because these reactions are reported voluntarily from a population of uncertain size, it is not always possible to estimate their frequency or establish a causal relationship to drug exposure.

Central and Peripheral Nervous System Disorders: burning sensation, including skin burning sensation

7 DRUG INTERACTIONS

7.1 Drugs Having Clinically Important Interactions with CAPLYTA

Clinically important drug interactions with CAPLYTA are presented in Table 6.

Table 6: Clinically Important Drug Interactions with CAPLYTA
CYP3A4 Inducers*
Prevention or Management | Avoid concomitant use of CAPLYTA with CYP3A4 inducers.
Clinical Impact | Concomitant use of CAPLYTA with CYP3A4 inducers decreases the exposure of lumateperone [see Clinical Pharmacology (12.3)].
Moderate or Strong CYP3A4 Inhibitors*
Prevention or Management | Reduce the CAPLYTA dosage when used concomitantly with moderate or strong CYP3A4 inhibitors [see Dosage and Administration (2.2)].
Clinical Impact | Concomitant use of CAPLYTA with moderate or strong CYP3A4 inhibitors increases lumateperone exposure [see Clinical Pharmacology (12.3)], which may increase the risk of adverse reactions.
Serotonin Reuptake Inhibitors
Prevention or Management | Increased monitoring for SRI- associated adverse reactions is recommended.
Clinical Impact | Although no clinically significant drug interactions with adjunctive SSRI/SNRIs in MDD were observed in CAPLYTA clinical trials, CAPLYTA’s moderate serotonin transporter (SERT) activity may increase the risk of SRI-associated adverse reactions (e.g., serotonin syndrome, hyponatremia).

* See www.fda.gov/CYPandTransporterInteractingDrugs for examples of CYP3A4 Inducers and Moderate or Strong CYP3A4 Inhibitors

8 USE IN SPECIFIC POPULATIONS

8.1 Pregnancy

Pregnancy Exposure Registry

There is a pregnancy exposure registry that monitors pregnancy outcomes in women exposed to atypical antipsychotics, including CAPLYTA, during pregnancy. Healthcare providers are encouraged to advise patients to register by calling the National Pregnancy Registry for Atypical Antipsychotics at 1-866-961-2388 or visiting online at https://womensmentalhealth.org/research/pregnancyregistry/.

Risk Summary

Neonates exposed to antipsychotic drugs during the third trimester are at risk for extrapyramidal and/or withdrawal symptoms following delivery (see Clinical Considerations). Available data from case reports on CAPLYTA use in pregnant women are insufficient to establish any drug associated risks for birth defects, miscarriage, or adverse maternal or fetal outcomes. There are risks to the mother associated with untreated schizophrenia and with exposure to antipsychotics, including CAPLYTA, during pregnancy (see Clinical Considerations). In animal reproduction studies, no malformations were observed with oral administration of lumateperone to pregnant rats and rabbits during organogenesis at doses up to 2.4 and 9.7 times, respectively, the maximum recommended human dose (MRHD) of 42 mg/day on a mg/m^2 basis. When pregnant rats were administered lumateperone during the period of organogenesis through lactation, the number of perinatal deaths of pups was increased at 4.9 times the MRHD, with no adverse effects on pups at 2.4 times the MRHD (see Data).

The estimated background risk of major birth defects and miscarriage for the indicated population is unknown. All pregnancies have a background risk of birth defect, loss, or other adverse outcomes. In the U.S. general population, the estimated background risk of major birth defects and miscarriage in clinically recognized pregnancies is 2 to 4% and 15 to 20%, respectively.

Clinical Considerations

Disease Associated Maternal and/or Embryo/fetal Risk: There is risk to the mother from untreated schizophrenia, including increased risk of relapse, hospitalization, and suicide. Schizophrenia is associated with increased adverse perinatal outcomes, including preterm birth. It is not known if this is a direct result of the illness or other comorbid factors.

Fetal/neonatal Adverse Reactions: Extrapyramidal and/or withdrawal symptoms, including agitation, hypertonia, hypotonia, tremor, somnolence, respiratory distress, and feeding disorder have been reported in neonates who were exposed to antipsychotic drugs during the third trimester of pregnancy. These symptoms have varied in severity. Monitor neonates for extrapyramidal and/or withdrawal symptoms and manage symptoms appropriately. Some neonates recovered within hours or days without specific treatment; others required prolonged hospitalization.

Data

Animal Data

Pregnant rats were treated with oral doses of 3.5, 10.5, 21, and 63 mg/kg/day lumateperone (0.8, 2.4, 4.9, and 14.6 times the MRHD on a mg/m^2 basis) during the period of organogenesis. No malformations were observed with lumateperone at doses up to 2.4 times the MRHD. Findings of decreased body weight were observed in fetuses at 4.9 and 14.6 times the MRHD. Findings of incomplete ossification and increased incidences of visceral and skeletal variations were recorded in fetuses at 14.6 times the MRHD, a dose that induced maternal toxicity.

Pregnant rabbits were treated with oral doses of 2.1, 7, and 21 mg/kg/day lumateperone (1.0, 3.2, and 9.7 times the MRHD on a mg/m^2 basis) during the period of organogenesis. Lumateperone did not cause adverse developmental effects at doses up to 9.7 times the MRHD.

In a study in which pregnant rats were administered oral doses of 3.5, 10.5, and 21 mg/kg/day lumateperone (0.8, 2.4, and 4.9 times the MRHD on a mg/m^2 basis) during the period of organogenesis and through lactation, the number of live-born pups was decreased at 2.4 and 4.9 times the MRHD, and early postnatal deaths increased at a dose 4.9 times the MRHD. Impaired nursing and decreased body weight gain in pups were observed at 4.9 times, but not at 2.4 times, the MRHD.

Pregnant rats were treated with a human metabolite of lumateperone (reduced ketone metabolite) at oral doses of 15, 60, and 100 mg/kg/day (1.2, 19, and 27 times the exposure to this metabolite at the MRHD of lumateperone based on AUC plasma exposure) during the period of organogenesis. This metabolite did not cause adverse developmental effects at a dose 1.2 times the exposure at the MRHD of lumateperone; however, it caused an increase in visceral malformations (cleft palate) at 27 times and skeletal malformations at 19 times the exposure at the MRHD of lumateperone, a dose that induced maternal toxicity.

8.2 Lactation

Risk Summary

Lumateperone and its metabolites are present in human breast milk in low amounts. In a clinical lactation study, lumateperone was detected in human milk at an estimated daily infant dose 0.0004 mg/kg, with a relative infant dose (RID) of 0.06% the maternal weight-adjusted dosage. Several major circulating metabolites were similarly detected in breast milk in low amounts; however, aniline metabolites were not present in milk or maternal plasma at quantifiable levels (see Data). There are no data on the effects of lumateperone on the breastfed infant or the effects on milk production.

The developmental and health benefits of breastfeeding should be considered along with the mother’s clinical need for CAPLYTA and any potential adverse effects on the breastfed child from CAPLYTA or from the underlying maternal condition.

Data

A lactation study in 17 lactating women evaluated the concentrations of lumateperone and its metabolites in plasma and mature breast milk following a single dose of 42 mg CAPLYTA. The estimated daily infant dose of lumateperone in human milk was 0.0004 mg/kg/day (with assumed average milk consumption of 200 ml/kg/day). The mean relative infant dose (RID) (with assumed mean milk consumption of 200 mL/kg/day and average maternal weight of 71 kg) was 0.06% of the maternal weight-adjusted dosage. Several major circulating metabolites were also present in breast milk at estimated daily infant dose of 0.0004 mg/kg/day. Aniline metabolites were not present in milk or maternal plasma at quantifiable levels.

8.3 Females and Males of Reproductive Potential

Infertility

Based on findings from animal studies, lumateperone may impair male and female fertility [see Nonclinical Toxicology (13.1)].

8.4 Pediatric Use

Safety and effectiveness of CAPLYTA have not been established in pediatric patients.

Antidepressants increased the risk of suicidal thoughts and behaviors in pediatric patients [see Boxed Warning, Warnings and Precautions (5.2)].

8.5 Geriatric Use

Controlled clinical studies of CAPLYTA for the treatment of schizophrenia and as adjunctive therapy with antidepressants for the treatment of MDD did not include any patients aged 65 or older to determine whether or not they respond differently from younger adult patients.

Among the CAPLYTA-treated patients in clinical studies for the treatment of depressive episodes associated with bipolar depression, 20 (6%) were 65 to 74 years of age, and none were 75 years of age or older [see Clinical Studies (14.2)]. These clinical studies did not include sufficient numbers of patients aged 65 years of age or older to determine whether or not they respond differently from younger adult patients.

Antipsychotic drugs increase the risk of death in elderly patients with dementia-related psychosis. CAPLYTA is not approved for the treatment of patients with dementia-related psychosis [see Boxed Warning, Warnings and Precautions (5.1) and (5.3)].

Elderly patients with dementia-related psychosis treated with antipsychotics have an increased risk of cerebrovascular adverse reactions (e.g., stroke, transient ischemic attack) including fatalities, compared to those treated with placebo [see Warnings and Precautions (5.1)].

Antipsychotic drugs increase the risk of tardive dyskinesia and this risk appears to be highest among the elderly, particularly elderly women [see Warnings and Precautions (5.5)].

The use of serotonin reuptake inhibitors (SRIs) has been associated with clinically significant hyponatremia in geriatric patients, who may be at greater risk for this adverse reaction. The concomitant use of CAPLYTA with an SRI may increase this risk [see Drug Interactions (7.1)].

8.6 Hepatic Impairment

Patients with moderate hepatic impairment (HI) (Child-Pugh class B) and severe HI (Child-Pugh class C) generally had higher exposure to lumateperone than patients with normal hepatic function; therefore, the recommended CAPLYTA dosage in patients with moderate or severe HI is lower than those with normal hepatic function [see Dosage and Administration (2.3) and Clinical Pharmacology (12.3)].

The recommended dosage in patients with mild HI (Child-Pugh class A) is the same as those with normal hepatic function.

10 OVERDOSAGE

No specific antidotes for CAPLYTA are known. In managing an CAPLYTA overdose, provide supportive care, including close medical supervision and monitoring and consider the possibility of multiple drug involvement. Consider contacting the Poison Help line (1-800-222-1222) or a medical toxicologist for additional overdose management recommendations.

11 DESCRIPTION

Lumateperone is an atypical antipsychotic present as lumateperone tosylate salt with the chemical name 4-((6bR,10aS)-3-methyl-2,3,6b,9,10,10a-hexahydro-1H,7H-pyrido[3',4':4,5]pyrrolo[1,2,3-de]quinoxalin-8-yl)-1-(4-fluoro-phenyl)-butan-1-one 4-methylbenzenesulfonate. Its molecular formula is C31H36FN3O4S, and its molecular weight is 565.71 g/mol with the following structure:

CAPLYTA (lumateperone) capsules are for oral administration. Each capsule contains:

- 42 mg of lumateperone (equivalent to 60 mg of lumateperone tosylate), or
- 21 mg of lumateperone (equivalent to 30 mg of lumateperone tosylate), or
- 10.5 mg of lumateperone (equivalent to 15 mg of lumateperone tosylate).

The capsules include the following inactive ingredients: croscarmellose sodium, gelatin, magnesium stearate, mannitol, and talc. Colorants include FD&C blue #1 and red #3 (42 mg), FDA/E172 black iron oxide, FDA/E172 red iron oxide and FD&C red #3 (10.5 mg), and titanium dioxide (42 mg, 21 mg and 10.5 mg).

12 CLINICAL PHARMACOLOGY

12.1 Mechanism of Action

The mechanism of action of lumateperone for the treatment of schizophrenia in adults, for the treatment of depressive episodes associated with bipolar depression (as monotherapy or as adjunctive therapy with lithium or valproate), and as adjunctive therapy with antidepressants for the treatment of MDD is unknown. However, the mechanism of action of lumateperone for these uses could be mediated through a combination of antagonist activity at central serotonin 5-HT2A receptors, and partial agonist activity at central dopamine D2 receptors.

12.2 Pharmacodynamics

Lumateperone has high binding affinity for serotonin 5-HT2A receptors (Ki = 0.54 nM) and moderate binding affinity for dopamine D2 (Ki = 32 nM) receptors. Lumateperone has moderate binding affinity for dopamine D1 (Ki = 41 nM) and D4 and adrenergic alpha1A and alpha1B receptors (Ki ≤ 100 nM), serotonin transporters (Ki = 33 nM), and inhibits uptake of serotonin in cells expressing the human SERT (IC50 = 150 nM). Lumateperone has low binding affinity (less than 50% inhibition at 100 nM) for muscarinic and histaminergic receptors.

In healthy human volunteers the mean cortical 5-HT2A receptor occupancy and the mean striatal D2 receptor occupancy were greater than 80% and approximately 12%, respectively, after a single 7 mg dose of CAPLYTA. D2 receptor occupancy increased with a dose from 7 mg to 28 mg. In patients with schizophrenia treated with CAPLYTA 42 mg for 2 weeks, mean dorsal striatal D2 receptor occupancy was 39%.

Cardiac Electrophysiology

QTcF interval was evaluated in a randomized, placebo- and active- (moxifloxacin 400 mg) controlled, four-arm crossover study utilizing concentration-QTc effect modeling in 33 patients with schizophrenia. The placebo-corrected change from baseline QTcF (90% two-sided upper confidence interval) values of 4.9 (8.9) and 15.8 (19.8) ms for a CAPLYTA 42 mg once daily oral dosage for five days and a CAPLYTA 126 mg once daily oral dosage (three times the recommended daily dosage) for five days, respectively.

12.3 Pharmacokinetics

Following once daily oral administration of CAPLYTA, lumateperone steady state is reached in about 5 days. Lumateperone steady-state exposure is approximately dose-proportional in the range of 3.5 mg to 56 mg (0.08 to 1.3 times the approved recommended daily dosage). A large inter-subject variability in lumateperone PK parameters was observed, with coefficients of variation for Cmax (peak plasma concentration) and AUC (area under the concentration vs time curve) ranging from 68% to 97% at steady state.

Absorption

After CAPLYTA dosing, the absolute bioavailability of lumateperone is about 4.4%. Cmax of lumateperone is reached approximately 1-2 hours after CAPLYTA dosing.

Effect of Food: Ingestion of a high-fat meal with CAPLYTA lowered lumateperone mean Cmax by 33% and increased mean AUC by 9%. Median Tmax was delayed about 1 hour (from 1 hour at fasted state to 2 hours in the presence of food).

Distribution

Protein binding of lumateperone is 97.4% at 5 µM (about 70-fold higher than therapeutic concentrations) in human plasma. The volume of distribution of lumateperone following intravenous administration is about 4.1 L/kg.

Elimination

The clearance of lumateperone is approximately 27.9 L/hour and the terminal half-life is about 18 hours after intravenous administration.

Metabolism: Lumateperone is extensively metabolized with more than twenty metabolites identified in vivo. After a single ^14C-labeled oral dose, lumateperone and glucuronidated metabolites represent about 2.8% and 51% of the total plasma radioactivity, respectively. In vitro studies show that multiple enzymes, including but not limited to uridine 5'-diphospho-glucuronosyltransferases (UDP-glucuronosyltransferase, UGT) 1A1, 1A4, and 2B15, aldoketoreductase (AKR)1C1, 1B10, and 1C4, and cytochrome P450 (CYP) 3A4, 2C8, and 1A2, are involved in the metabolism of lumateperone.

Excretion: In a human mass‑balance study, 58% and 29% of the radioactive dose was recovered in the urine and feces, respectively. Less than 1% of the dose was excreted as unchanged lumateperone in the urine.

Specific Populations

No clinically significant differences in the pharmacokinetics of lumateperone were observed based on age, sex, or race.

Patients with Hepatic Impairment: The pharmacokinetics of lumateperone were evaluated in patients with varying degrees of hepatic impairment (HI) and in those with normal hepatic function following administration of a single 14 mg dose of CAPLYTA. Table 7 displays the geometric mean ratios (90% confidence intervals) of lumateperone pharmacokinetic parameters in CAPLYTA-treated patients with varying degrees of HI to those with normal hepatic function [see Use in Specific Populations (8.6)].

Table 7: Geometric Mean Ratios (90% confidence interval) of Lumateperone Pharmacokinetic Parameters in CAPLYTA-treated Patients with Hepatic Impairment
 | AUCt | Cmax
Mild HI (Child-Pugh Class A) | 1.1 (0.8, 1.7) | 1.4 (0.8, 2.3)
Moderate HI (Child-Pugh Class B) | 2.4 (1.6, 3.6) | 2 (1.2, 3.2)
Severe HI (Child-Pugh Class C) | 1.8 (1.2, 2.8) | 1.6 (0.9, 2.6)

Patients with Renal Impairment: The pharmacokinetics of lumateperone were evaluated in patients with varying degrees of renal impairment (RI) and in those with normal renal function following administration of a single 14 mg dose of CAPLYTA. Table 8 displays the geometric mean ratios (90% confidence intervals) of lumateperone pharmacokinetic parameters in CAPLYTA-treated patients with varying degrees of RI to those with normal renal function (eGFR > 90 mL/minute/1.73 m^2).

Table 8: Geometric Mean Ratios (90% confidence interval) of Lumateperone Pharmacokinetic Parameters in CAPLYTA-treated Patients with Renal Impairment
 | AUCt | Cmax
Mild RI (eGFR of 60 - 89 mL/minute/1.73 m^2) | 0.54 (0.31, 0.92) | 0.62 (0.35, 1.10)
Moderate RI (eGFR of 30 - 59 mL/minute/1.73 m^2) | 1 (0.6, 1.8)* | 1 (0.6, 1.9)*
Severe RI (eGFR ≤ 29 mL/minute/1.73 m^2) | 1.5 (0.8, 2.6) | 1.4 (0.8, 2.4)

* The pharmacokinetics were unchanged.

Drug Interaction Studies

Clinical Studies:

Strong CYP3A4 Inhibitors: Itraconazole (strong CYP3A4 inhibitor) increased geometric mean (90% confidence interval) of lumateperone AUCt by 3.8-fold (3.2, 4.5) and lumateperone Cmax by 3.2-fold (2.8 – 3.7) [see Drug Interactions (7.1)]

Moderate CYP3A4 Inhibitors: Diltiazem (moderate CYP3A4 inhibitor) increased geometric mean (90% confidence interval) of lumateperone AUCt by 2.3-fold (1.6, 3.3) and lumateperone Cmax by 1.9-fold (1.3, 2.6) [see Drug Interactions (7.1)]

Strong CYP3A4 Inducers: Rifampin (strong CYP3A4 inducer) decreased geometric mean (90% confidence interval) of lumateperone AUCt by 98% (96%, 99%) and lumateperone Cmax by 92% (87%, 95%) [see Drug Interactions (7.1)]

UGT inhibitors: There were no clinically significant drug interactions with the UGT inhibitors probenecid and valproic acid.

CYP3A4 substrates: No clinically significant differences in the pharmacokinetics of midazolam (CYP3A4 substrate) or its metabolite 1-hydroxymidazolam were observed when used concomitantly with single or multiple doses of lumateperone in patients with schizophrenia.

In Vitro Studies:

Lumateperone showed little to no inhibition of CYP1A2, CYP2C9, CYP2C19, CYP2D6, or CYP3A4/5. It showed no induction of CYP1A2, CYP2B6, or CYP3A4.

Lumateperone did not appear to be a P-gp or BCRP substrate. It showed little to no inhibition of OCT2, OAT1, OAT3, OATP1B3, or OATP1B1.

13 NONCLINICAL TOXICOLOGY

13.1 Carcinogenesis, Mutagenesis, Impairment of Fertility

Carcinogenesis

Lifetime carcinogenicity studies were conducted in rats and mice, and results showed no carcinogenic potential in either species.

In Sprague-Dawley rats, males were administered lumateperone (free base) at oral doses of 3.5, 7 or 14 mg/kg/day and females were administered lumateperone at oral doses of 3.5, 10.5, or 21 mg/kg/day for the first 385 days, then doses were reduced for the two higher dose groups so that the females were administered 3.5, 7 or 14 mg/kg/day, respectively, for the duration of the study. In this study the no adverse effect level for neoplastic lesions was determined to be 14 mg/kg/day (84 mg/m^2/day) for males and 10.5/7 mg/kg/day (42 mg/m^2/day) for females, which are 1.6 times (females) to 3.2 times (males) the MRHD on a mg/m^2 basis.

Male and female CD-1 mice were administered lumateperone at oral doses of 3.5, 10.5 or 21 mg/kg/day for the first 35 days, then doses were reduced to 1.4, 4.9, and 14 mg/kg/day, respectively, for the duration of the study. In this study, the no adverse effect level for neoplastic lesions was determined to be 10.5/4.9 mg/kg/day (15 mg/m^2/day) for each sex which is 0.6 times the MRHD on a mg/m^2 basis.

Mutagenesis

No evidence of mutagenic potential was found in the in vitro bacterial reverse mutation assay (Ames test) and the mouse lymphoma test without metabolic activation. Lumateperone was positive in the Ames test only in the presence of metabolic activation and only in the TA1537 strain and was positive in the mouse lymphoma test only in the presence of metabolic activation and only at high concentrations that inhibited cell growth; together these results were thought to be related to solubility limits and/or nonspecific effects on cellular function. Lumateperone was negative for clastogenic activity in the in vivo micronucleus assay in rats and was not genotoxic in the in vivo Comet assay in rats.

Impairment of Fertility

Female rats were treated with oral doses of 3.5, 10.5, 21 or 42 mg/kg/day lumateperone (free base) (0.8, 2.4, 4.9, and 9.7 times the MRHD on a mg/m^2 basis) prior to mating and continuing through conception and implantation. Estrus cycle irregularities were observed at doses ≥10.5 mg/kg/day. Decreases in the median number of corpora lutea and implantation sites, and increases in the number of non-gravid uteruses, were recorded at 42 mg/kg/day. Decreased gestation body weight and body weight gain, and increases in time to mating, were observed at 21 and 42 mg/kg/day.

Male rats were treated with oral doses of 3.5, 10.5, 21 or 42 mg/kg/day lumateperone (0.8, 2.4, 4.9, and 9.7 times the MRHD on a mg/m^2 basis) for 9 weeks prior to mating and throughout 14 days of mating. Decreased sperm motility, changes in sperm morphology, reduced epididymal counts, and adverse histopathology changes in testes and epididymides were observed at 21 and 42 mg/kg/day.

13.2 Animal Toxicology and/or Pharmacology

Oral administration of lumateperone caused systemic intracytoplasmic accumulation of pigmented material in dogs, rats, and mice at clinically relevant exposures (AUC). Intracytoplasmic pigmentation appeared to be localized in lysosomes. Accumulation of pigmented material persisted without reversal at the end of 1- to 2-month drug-free periods. Pigmented material was observed in the brain and spinal cord of all three species, and in the heart and eye of rats. Although the composition of the pigmented material was not established, the material is likely polymers or protein adducts formed from aniline metabolites of lumateperone.

In the dog, accumulation of pigmented material in the brain and spinal cord was associated with neuronal degeneration and necrosis, followed by axonal degeneration and histiocytic inflammation after oral administration of lumateperone for up to 9 months. In the rat, accumulation of pigmented material was associated with degenerative changes and signs of an inflammatory response in the spinal cord, peripheral nervous system, eye, and heart after oral administration of lumateperone for up to 2 years. Although overt degenerative changes were not observed in the rat brain, the presence of pigment-containing infiltrating macrophages is consistent with an inflammatory response.

The role of intracytoplasmic pigmented material in causing these lesions was not definitively established; however, the colocalization of pigmented material in tissues with degenerative changes and signs of inflammation is supportive. Alternatively, the aniline metabolites of lumateperone may undergo metabolic activation forming reactive metabolites that contribute to the observed toxicities. The role of intracellular accumulation of lumateperone or its non-aniline metabolites in these toxicities could not be ruled out.

The aniline metabolites thought to be responsible for these toxicities were detected in dogs and rats but were not present in humans at quantifiable levels. Based on all the available evidence, these toxicities do not appear to be relevant to humans.

14 CLINICAL STUDIES

14.1 Schizophrenia

CAPLYTA was evaluated for the treatment of schizophrenia in adults in two placebo-controlled trials (i.e., Studies 1 and 2).

Study 1 (Adults with Schizophrenia)

Study 1 Design: Study 1 (NCT01499563) was a four-week, randomized, double-blind, placebo-controlled, multi-center study in adult patients with a diagnosis of schizophrenia according to the DSM-IV-TR criteria. The primary efficacy measure was change from baseline in the Positive and Negative Syndrome Scale (PANSS) total score at Week 4. The PANSS is a 30-item scale used to measure symptoms of schizophrenia. Each item is rated by a clinician on a seven-point scale. A score of 1 indicates the absence of symptoms, and a score of 7 indicates extremely severe symptoms. The PANSS total score ranges from 30 to 210 with higher scores reflecting greater overall symptom severity.

A total of 335 patients were randomized to receive oral CAPLYTA 42 mg, CAPLYTA 84 mg (two times the recommended daily dose), an active comparator, or placebo once daily. The study was not designed to allow for efficacy comparison of CAPLYTA and the active comparator.

Study 1 Baseline Demographics: Demographic and baseline disease characteristics were similar for the CAPLYTA, active comparator, and placebo groups. Median age was 42 years (range 20 to 55 years). 17% were female, 19% were White, and 78% were Black.

Study 1: Summary of Primary Efficacy Results: Compared to the placebo group, patients randomized to CAPLYTA 42 mg once daily showed a statistically significant reduction from baseline to Day 28 in the PANSS total score. The treatment effect in the CAPLYTA 84 mg once daily treatment group (vs. placebo group) was not statistically significant. The results of Study 1 are shown in Table 9.

Study 2 (Adults with Schizophrenia)

Study 2 Design: Study 2 (NCT02282761) was a four-week, randomized, double-blind, placebo-controlled, multi-center study in adult patients with a diagnosis of schizophrenia according to the DSM-5 criteria. The primary efficacy measure was change from baseline in the PANSS total score at Week 4.

A total of 450 patients were randomized to receive oral CAPLYTA 28 mg (two-thirds the recommended daily dose), CAPLYTA 42 mg, or placebo once daily.

Study 2 Baseline Demographics: Demographic and baseline disease characteristics were similar for the CAPLYTA and placebo groups. Median age was 44 years (range 19 to 60 years); 23% were female, 26% were White and 66% were Black.

Study 2: Summary of Primary Efficacy Results: Compared to the placebo group, patients in the CAPLYTA 42 mg group showed a statistically significant reduction from baseline to Day 28 in the PANSS total score. The treatment effect in the CAPLYTA 28 mg group (vs. placebo group) was not statistically significant. The results of Study 2 are shown in Table 9.

Efficacy Results in Studies 1 and 2 (Adults with Schizophrenia)

Studies 1 and 2 did not include any patients aged 65 or older. Examination of subgroups by sex and race did not suggest differences in response in either study.

Table 9: Primary Efficacy Results for Change from Baseline in PANSS Total Score in Adult Patients with Schizophrenia (Studies 1 and 2)
 |  |  | Primary Efficacy Endpoint: PANSS Total Score
Study Number | Treatment Group | N | Mean Baseline Score (SD) | LS Mean Change; from Baseline (SE) | Placebo-subtracted; Difference; (95% CI)
1 | CAPLYTA (42 mg once daily)* | 84 | 88.1 (11.0) | -13.2 (1.7) | -5.8 (-10.5, -1.1)a
1 | Placebo | 85 | 86.3 (13.1) | -7.4 (1.7) | --
2 | CAPLYTA (42 mg once daily)* | 150 | 90.0 (9.6) | -14.5 (1.3) | -4.2 (-7.8, -0.6)
2 | Placebo | 150 | 89.0 (10.3) | -10.3 (1.3) | --

The PANSS total score may range from 30 to 210; higher scores reflect greater symptom severity.
SD: standard deviation; SE: standard error; LS Mean: least squares mean; CI: unadjusted confidence interval.
aDifference (CAPLYTA minus placebo) in LS mean change from baseline not adjusted for sample size increase after unblinded interim analysis.
*CAPLYTA statistically significantly superior to placebo.

Figure 1: Change from Baseline in PANSS Total Score by Time (Weeks) in Adult Patients with Schizophrenia in Study 2.

14.2 Depressive Episodes Associated with Bipolar I or II Disorder (Bipolar Depression)

Clinical Study of CAPLYTA Monotherapy for Bipolar I or II Disorder

Study 3 Design: The efficacy of CAPLYTA, as monotherapy, for the treatment of depressive episodes associated with bipolar I or II disorder (bipolar depression) in adults was established in a 6-week, randomized, double-blind, placebo-controlled, multi-center study in adult patients who met DSM-5 criteria for depressive episodes associated with bipolar I or bipolar II disorder (Study 3; NCT03249376). The primary efficacy measure was the change from baseline in Montgomery-Asberg Depression Rating Scale (MADRS) total score at Week 6. The MADRS is a 10-item clinician-rated scale with total scores ranging from 0 (no depressive features) to 60 (maximum score). The secondary endpoint was the change from baseline in Clinical Global Impression-Bipolar-Severity of Illness scale (CGI-BP-S) total score at Week 6. The CGI-BP-S total score is a clinician-rated scale that measures the patient’s current illness state on a 21-point scale that assesses depression, mania, and overall illness, where a higher score is associated with greater illness severity.

A total of 381 patients were randomized to receive oral CAPLYTA 42 mg or placebo once daily.

Study 3 Baseline Demographic Characteristics: Demographic and baseline characteristics were similar for the CAPLYTA and placebo groups. Median age was 45 (range 18 to 72). 58% were female, 91% were White, and 8% were Black.

Study 3 Efficacy Results: Compared to the placebo group, patients in the CAPLYTA 42 mg group showed a statistically significant improvement from baseline to Day 43 in the MADRS total score and CGI-BP-S total score. The results of Study 3 are shown in Table 10.

Examination of subgroups by age, sex, and race did not suggest differences in response in the study.

Clinical Study of CAPLYTA Adjunctive Therapy with Lithium or Valproate for Bipolar I or II Disorder

Study 4 Design: The efficacy of CAPLYTA, as adjunctive therapy with lithium or valproate, for the treatment of depressive episodes associated with bipolar I or II disorder in adults was established in a 6-week, randomized, double-blind, placebo-controlled, multi-center study in adult patients who met DSM-5 criteria for depressive episodes associated with bipolar I or bipolar II disorder (Study 4; NCT02600507). The primary efficacy measure was the change from baseline in MADRS total score at Week 6. The secondary endpoint was the change from baseline in CGI-BP-S depression score at Week 6. The CGI-BP-S depression score is a clinician-rated scale that measures the patient’s current illness state on a 7-point scale, where a higher score is associated with greater illness severity.

A total of 529 patients were randomized to receive oral CAPLYTA 28 mg (two-thirds the recommended daily dosage), CAPLYTA 42 mg, or placebo once daily. Patients in all treatment groups continued treatment with lithium or valproate.

Study 4 Baseline Demographic Characteristics: Demographic and baseline characteristics were similar for the CAPLYTA and placebo groups. Median age was 46 (range 18 to 74). 58% were female, 88% were White, and 11% were Black.

Study 4 Efficacy Results: Compared to the placebo + lithium or valproate group, patients in the CAPLYTA 42 mg + lithium or valproate group showed a statistically significant improvement from baseline to Day 43 in the MADRS total score and CGI-BP-S depression score. The treatment effect in the CAPLYTA 28 mg + lithium or valproate group (vs. placebo + lithium or valproate group) was not statistically significant. The results of Study 4 are shown in Table 10.

Examination of subgroups by age, sex, and race did not suggest differences in response in the study.

Table 10: Primary Efficacy Results from Bipolar Depression Trials (Studies 3 and 4)
 |  |  |  | Primary Efficacy Endpoint: MADRS Total Score
Study Number | Treatment Group | N |  | Mean Baseline Score (SD) | LS Mean Change from Baseline (SE) | Placebo-subtracted Differencea (95% CI)
Monotherapy
3 | CAPLYTA (42 mg) once daily* | 188 |  | 30.8 (4.9) | -16.7 (0.7) | -4.6 (-6.3, -2.8)
3 | Placebo | 188 |  | 30.3 (4.6) | -12.1 (0.7)
Adjunctive Therapy
4 | CAPLYTA (42 mg) once daily* + lithium or valproate | 174 |  | 32.2 (5.0) | -16.9 (0.8) | -2.4 (-4.4, -0.4)
4 | Placebo + lithium or valproate | 174 |  | 32.1 (5.2) | -14.5 (0.8)

The MADRS total score ranges from 0 to 60; higher scores reflect greater symptom severity
SD: standard deviation; SE: standard error; LS Mean: least squares mean; CI: confidence interval
a Difference (CAPLYTA minus placebo) in LS mean change from baseline
* CAPLYTA statistically significantly superior to placebo.

Figure 2. Change from Baseline in MADRS Total Score by Visits (Study 3) in Adult Patients with Depressive Episodes Associated with Bipolar I or II Disorder (Monotherapy)

14.3 Adjunctive Treatment of Major Depressive Disorder in Adults

Studies 5 and 6 Designs: The effectiveness of CAPLYTA, as adjunctive therapy with antidepressants, for the treatment of major depressive disorder (MDD) in adults was established in two 6-week, randomized, double-blind, placebo-controlled, multi-center trials in adult patients who met DSM-5 criteria for MDD, with or without symptoms of anxiety who had inadequate response to one to two courses of prior antidepressant therapy (ADT) (Study 5 NCT04985942 and Study 6 NCT05061706). Inadequate response to ADT was defined as having less than 50% improvement after at least six weeks of treatment with selective serotonin or serotonin norepinephrine reuptake inhibitors or bupropion at the minimum effective ADT dosage or greater. Patients were randomized to receive oral CAPLYTA 42 mg or placebo once daily and all patients continued their background ADT.

Studies 5 and 6 Endpoints: In Study 5 and 6, the primary endpoint was change from baseline to Week 6 in the Montgomery-Asberg Depression Rating Scale (MADRS) total score [see Clinical Studies (14.2)] in the CAPLYTA + ADT group compared to the placebo + ADT group. The key secondary endpoint was the change from baseline to Week 6 in the Clinical Global Impression Scale-Severity (CGI-S) score. The CGI-S is a validated clinician-rated scale that measures the patient’s current illness state on a 1 (normal, not at all ill) to 7-point (extremely ill) scale.

Studies 5 and 6 Baseline Demographics:

- In Study 5, a total of 485 patients were randomized to receive CAPLYTA 42 mg + ADT or placebo + ADT. Demographic and baseline characteristics were similar for the CAPLYTA and placebo groups. Median age was 46 (range 18 to 65). 66% were female, 77% were White, 15% were Asian, and 7% were Black.
- In Study 6, a total of 480 patients were randomized to receive CAPLYTA 42 mg + ADT or placebo + ADT. Demographic and baseline characteristics were similar for the CAPLYTA and placebo groups. Median age was 48 (range 18 to 65). 70% were female, 95% were White.

Studies 5 and 6 Efficacy Results: In Studies 5 and 6, patients randomized to CAPLYTA 42 mg + ADT showed a statistically significant improvement from baseline to day 43 in the MADRS total score and CGI-S score compared to the placebo + ADT group. The results of Study 5 and Study 6 are shown in Table 11.

Examination of subgroups by age, sex, race, and ADT class did not suggest differences in response in these studies.

Table 11: Primary Efficacy Results from Adjunctive MDD Trials (Studies 5 and 6)
 |  |  | Primary Efficacy Endpoint: MADRS Total Score
Study Number | Treatment Group | N | Mean Baseline Score (SD) | LS Mean Change from Baseline (SE) | Placebo-subtracted Differencea (95% CI)
5 | CAPLYTA (42 mg) + ADT* | 239 | 30.4 (3.75) | -14.7 (0.54) | -4.9 (-6.38, -3.44)
5 | Placebo + ADT | 242 | 30.1 (3.50) | -9.8 (0.53)
6 | CAPLYTA (42 mg) + ADT* | 232 | 30.8 (3.88) | -14.7 (0.56) | -4.5 (-6.03, -3.02)
6 | Placebo + ADT | 237 | 31.5 (3.97) | -10.2 (0.54)

The MADRS total score ranges from 0 to 60; higher scores reflect greater symptom severity
SD: standard deviation; SE: standard error; LS Mean: least squares mean; CI: confidence interval
a Difference (CAPLYTA + ADT minus placebo + ADT) in LS mean change from baseline
* CAPLYTA + ADT statistically significantly superior to placebo + ADT.

The change from baseline in MADRS total score over time in adult patients who received adjunctive treatment for MDD in Study 5 is displayed in Figure 3.

Figure 3. Change from Baseline in MADRS Total Score by Time (Weeks) in Patients with MDD (Adjunctive Treatment) in Study 5

16 HOW SUPPLIED/ STORAGE AND HANDLING

CAPLYTA (lumateperone) capsules are supplied as follows:

Capsule Strength | Capsule Color | Imprint Codes |  | Package Configuration | NDC Code
42 mg | Blue cap and opaque white body | ITI-007 42 mg |  | Bottle of 30 | 72060-142-40
21 mg | Opaque white cap and body | ITI-007 21 mg |  | Bottle of 30 | 72060-121-40
10.5 mg | Opaque light pink cap and body | ITI-007 10.5 mg |  | Bottle of 30 | 72060-110-40

Store at controlled room temperature 20°C to 25°C (68°F to 77°F); excursions permitted to 15°C to 30°C (59°F to 86°F) [see USP Controlled Room Temperature].

17 PATIENT COUNSELING INFORMATION

Advise the patient or caregiver to read the FDA-approved patient labeling (Medication Guide).

Suicidal Thoughts and Behavior

Advise patients and caregivers to look for the emergence of suicidal thoughts and behaviors, especially early during CAPLYTA treatment and instruct them to report such symptoms to their healthcare provider [see Boxed Warning, Warnings and Precautions (5.2)].

Neuroleptic Malignant Syndrome

Counsel patients about a potentially fatal neuroleptic malignant syndrome (NMS), that has been reported with administration of antipsychotic drugs. Advise patients, family members, or caregivers to contact the healthcare provider or to report to the emergency room if they experience signs and symptoms of NMS [see Warnings and Precautions (5.4)].

Tardive Dyskinesia

Counsel patients on the signs and symptoms of tardive dyskinesia and to contact their healthcare provider if these abnormal movements occur [see Warnings and Precautions (5.5)].

Metabolic Changes

Educate patients about the risk of metabolic changes, how to recognize symptoms of hyperglycemia and diabetes mellitus, and the need for specific monitoring, including blood glucose, lipids, and weight [see Warnings and Precautions (5.6)].

Leukopenia/Neutropenia

Advise patients with a pre-existing low WBC or a history of drug induced leukopenia/ neutropenia that they should have their CBC monitored while taking CAPLYTA [see Warnings and Precautions (5.7)].

Orthostatic Hypotension and Syncope

Educate patients about the risk of orthostatic hypotension and syncope, especially early in treatment, and also at times of re-initiating treatment [see Warnings and Precautions (5.8)].

Effects on Driving and Operating Heavy Machinery

Caution patients about performing activities requiring mental alertness, such as operating hazardous machinery or operating a motor vehicle, until they are reasonably certain that CAPLYTA therapy does not affect them adversely [see Warnings and Precautions (5.11)].

Heat Exposure and Dehydration

Educate patients regarding appropriate care in avoiding overheating and dehydration [see Warnings and Precautions (5.12)].

Concomitant Drugs

Advise patients to inform their health care providers of any changes to their current prescription or over-the-counter drugs because there is a potential for clinically significant interactions [see Drug Interactions (7.1)].

Pregnancy

Advise patients to notify their healthcare provider if they become pregnant or intend to become pregnant during treatment with CAPLYTA. Advise patients that CAPLYTA used during the third trimester may cause extrapyramidal and/or withdrawal symptoms (agitation, hypertonia, hypotonia, tremor, somnolence, respiratory distress, and feeding disorder) in the neonate. Advise patients that there is a pregnancy registry that monitors pregnancy outcomes in women exposed to CAPLYTA during pregnancy [see Use in Specific Populations (8.1)].

Infertility

Advise males and females of reproductive potential that CAPLYTA may impair fertility [see Use in Specific Populations (8.3)].

Distributed by Intra-Cellular Therapies, Inc.

Bedminster, NJ 07921

CAPLYTA is a registered trademark of Intra-Cellular Therapies, Inc.

© 2025 Intra-Cellular Therapies, Inc. All rights reserved.

MEDICATION GUIDE

CAPLYTA (kap-LITE-ah)

(lumateperone) capsules, for oral use

What is the most important information I should know about CAPLYTA?

CAPLYTA may cause serious side effects, including:

- Increased risk of death in elderly people with dementia related psychosis. Medicines like CAPLYTA can raise the risk of death in elderly people who have lost touch with reality (psychosis) due to confusion and memory loss (dementia). CAPLYTA is not approved for the treatment of people with dementia-related psychosis.
- Increased risk of suicidal thoughts and actions. CAPLYTA and antidepressant medicines increase the risk of suicidal thoughts and actions in people 24 years of age and younger, especially within the first few months of treatment or when the dose is changed.
  - Depression and other mental illnesses are the most important causes of suicidal thoughts and actions.
  How can I watch for and try to prevent suicidal thoughts and actions in myself or a family member?
  - Pay close attention to any changes, especially sudden changes in mood, behaviors, thoughts, or feelings. This is very important when CAPLYTA or the antidepressant medicine is started or when the dose is changed.
  - Call your healthcare provider right away to report new or sudden changes in mood, behavior, thoughts, or feelings, or if you develop suicidal thoughts or actions.
  - Keep all follow-up visits with your healthcare provider as scheduled. Call your healthcare provider between visits as needed, especially if you have concerns about symptoms.
  Call a healthcare provider right away if you or your family member have any of the following symptoms, especially if they are new, worse, or worry you:

• thoughts about suicide or dying

• suicide attempts

• new or worse depression

• new or worse anxiety

• feeling very agitated or restless

• panic attacks

• trouble sleeping

• new or worse irritability

• acting aggressive, being angry, or violent

• acting on dangerous impulses

• an extreme increase in activity and talking (mania)

• other unusual changes in behavior or mood

See “What are the possible side effects of CAPLYTA?” for more information about side effects.

What is CAPLYTA?

CAPLYTA is a prescription medicine used in adults:

- to treat schizophrenia
- alone or along with the medicine lithium or valproate to treat depressive episodes that happen with bipolar I or bipolar II disorder (bipolar depression)
- along with antidepressant medicines to treat major depressive disorder (MDD)

It is not known if CAPLYTA is safe and effective in children.

Who should not take CAPLYTA?

Do not take CAPLYTA if you:

- are allergic to lumateperone or any of the ingredients in CAPLYTA. See the end of this Medication Guide for a complete list of ingredients in CAPLYTA.

Before taking CAPLYTA, tell your healthcare provider about all of your medical conditions, including if you:

- have or have had heart problems or a stroke
- have or have had low or high blood pressure
- have or have had diabetes or high blood sugar, or a family history of diabetes or high blood sugar.
- have or have had high levels of total cholesterol, LDL cholesterol, or triglycerides or low levels of HDL cholesterol
- have or have had a low white blood cell count
- have or have had seizures (convulsions)
- have or have had kidney or liver problems
- are pregnant or plan to become pregnant. CAPLYTA may harm your unborn baby. Taking CAPLYTA during your third trimester of pregnancy may cause your baby to have abnormal muscle movements or withdrawal symptoms after birth. Talk to your healthcare provider about the risk to your unborn baby if you take CAPLYTA during pregnancy.
  - Tell your healthcare provider if you become pregnant or think you are pregnant during treatment with CAPLYTA.
  - There is a pregnancy registry for females who are exposed to CAPLYTA during pregnancy. If you become pregnant during treatment with CAPLYTA, talk to your healthcare provider about registering with the National Pregnancy Registry for Atypical Antipsychotics. You can register by calling 1-866-961-2388 or go to https://womensmentalhealth.org/research/pregnancyregistry/.
- are breastfeeding or plan to breastfeed. CAPLYTA passes into your breast milk. Talk to your healthcare provider about the risks and benefits of breastfeeding and the best way to feed your baby during treatment with CAPLYTA.

Tell your healthcare provider about all the medicines you take, including prescription and over-the-counter medicines, vitamins, and herbal supplements.

CAPLYTA and other medicines may affect each other causing possible serious side effects. CAPLYTA may affect the way other medicines work, and other medicines may affect how CAPLYTA works.

Your healthcare provider can tell you if it is safe to take CAPLYTA with your other medicines. Do not start or stop any medicines during treatment with CAPLYTA without first talking to your healthcare provider.

Know the medicines you take. Keep a list of your medicines to show your healthcare provider and pharmacist when you get a new medicine.

How should I take CAPLYTA?

- Take CAPLYTA exactly as your healthcare provider tells you to take it. Do not change the dose or stop taking CAPLYTA without first talking to your healthcare provider.
- Take CAPLYTA 1 time each day with or without food.
- If you take too much CAPLYTA, call your healthcare provider or Poison Help Line at 1-800-222-1222 or go to the nearest hospital emergency room right away.

What should I avoid while taking CAPLYTA?

- Do not drive, operate machinery, or do other dangerous activities until you know how CAPLYTA affects you. CAPLYTA may make you drowsy.
- Do not become too hot or dehydrated during treatment with CAPLYTA.
  - Do not exercise too much.
  - In hot weather, stay inside in a cool place if possible.
  - Stay out of the sun.
  - Do not wear too much clothing or heavy clothing.
  - Drink plenty of water.

What are the possible side effects of CAPLYTA?

CAPLYTA may cause serious side effects, including:

- See “What is the most important information I should know about CAPLYTA?”
- Stroke (cerebrovascular problems) in elderly people with dementia-related psychosis that can lead to death.
- Neuroleptic malignant syndrome (NMS) is a serious condition that can lead to death. Call your healthcare provider or go to the nearest hospital emergency room right away if you have some or all of the following signs and symptoms of NMS:

◦ high fever

◦ confusion

◦ changes in your breathing, heart rate, and blood pressure

◦ stiff muscles

◦ increased sweating

- Uncontrolled body movements (tardive dyskinesia). CAPLYTA may cause movements that you cannot control in your face, tongue, or other body parts. Tardive dyskinesia may not go away, even if you stop taking CAPLYTA. Tardive dyskinesia may also start after you stop taking CAPLYTA.
- Problems with your metabolism such as:
  - high blood sugar (hyperglycemia) and diabetes. Increases in blood sugar can happen in some people who take CAPLYTA. Extremely high blood sugar can lead to coma or death. Your healthcare provider should check your blood sugar before you start, or soon after you start CAPLYTA, and then regularly during long term treatment with CAPLYTA.
  Call your healthcare provider if you have any of these symptoms of high blood sugar during treatment with CAPLYTA:

• feel very thirsty

• need to urinate more than usual

• feel very hungry

• feel weak or tired

• feel sick to your stomach

• feel confused, or your breath smells fruity

- increased fat levels (cholesterol and triglycerides) in your blood. Your healthcare provider should check the fat levels in your blood before you start, or soon after you start CAPLYTA, and then periodically during treatment with CAPLYTA.
- weight gain. You and your healthcare provider should check your weight before you start and often during treatment with CAPLYTA.

- Low white blood cell count. Your healthcare provider may do blood tests during the first few months of treatment with CAPLYTA.
- Decreased blood pressure (orthostatic hypotension). You may feel lightheaded or faint when you rise too quickly from a sitting or lying position.
- Falls. CAPLYTA may make you sleepy or dizzy, may cause a decrease in your blood pressure when changing position (orthostatic hypotension), and can slow your thinking and motor skills which may lead to falls that can cause fractures or other injuries.
- Seizures (convulsions).
- Sleepiness, drowsiness, feeling tired, difficulty thinking and doing normal activities. See "What should I avoid while taking CAPLYTA?"
- Problems controlling your body temperature so that you feel too warm. See “What should I avoid while taking CAPLYTA?”
- Difficulty swallowing that can cause food or liquid to get into your lungs.

The most common side effects of CAPLYTA include sleepiness, dizziness, nausea, dry mouth, feeling tired, and diarrhea.

CAPLYTA may cause fertility problems in females and males. Talk to your healthcare provider if this is a concern for you.

These are not all the possible side effects of CAPLYTA.

Call your doctor for medical advice about side effects. You may report side effects to FDA at 1-800-FDA-1088.

How should I store CAPLYTA?

• Store CAPLYTA at room temperature between 68°F to 77°F (20°C to 25°C).

Keep CAPLYTA and all medicines out of the reach of children.

General information about the safe and effective use of CAPLYTA.

Medicines are sometimes prescribed for purposes other than those listed in a Medication Guide. Do not use CAPLYTA for a condition for which it was not prescribed. Do not give CAPLYTA to other people, even if they have the same symptoms that you have. It may harm them. You can ask your pharmacist or healthcare provider for information about CAPLYTA that is written for health professionals.

What are the ingredients in CAPLYTA?

Active ingredient: lumateperone

Inactive ingredients: croscarmellose sodium, gelatin, magnesium stearate, mannitol, and talc. Colorants include FD&C blue #1 and red #3 (42 mg), FDA/E172 black iron oxide, FDA/E172 red iron oxide and FD&C red #3 (10.5 mg), and titanium dioxide (42 mg, 21 mg and 10.5 mg).

Distributed by: Intra-Cellular Therapies, Inc., Bedminster, NJ 07921

©2025 Intra-Cellular Therapies, Inc. All rights reserved.

For more information, go to www.CAPLYTA.com or call (888) 252-4824

This Medication Guide has been approved by the U.S. Food and Drug Administration. Revised:11/2025

PRINCIPAL DISPLAY PANEL

42 mg 30 Count Bottle Label

Rx Only

30 capsules

NDC 72060-142-40

21 mg 30 Count Bottle Label

Rx Only

30 capsules

NDC 72060-121-40

10.5 mg 30 Count Bottle Label

Rx Only

30 capsules

NDC 72060-110-40

42 mg 7 Count Sample Carton

Professional Sample.

Not for Sale.

NDC 72060-142-07

21 mg 7 Count Sample Carton

Professional Sample.

Not for Sale.

NDC 72060-121-07

10.5 mg 7 Count Sample Carton

Professional Sample.

Not for Sale.

NDC 72060-110-07